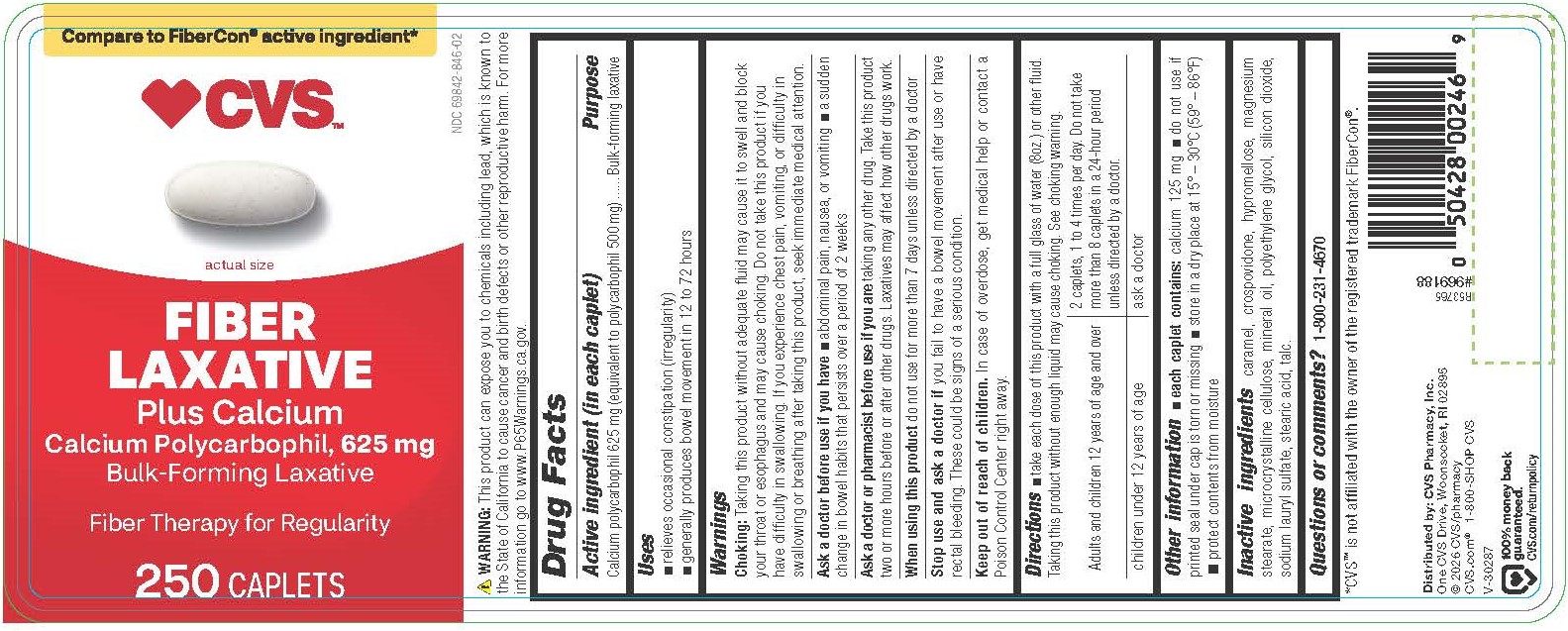 DRUG LABEL: Calcium Polycarbophil
NDC: 69842-846 | Form: TABLET, FILM COATED
Manufacturer: CVS Pharmacy, Inc
Category: otc | Type: HUMAN OTC DRUG LABEL
Date: 20260127

ACTIVE INGREDIENTS: CALCIUM POLYCARBOPHIL 625 mg/1 1
INACTIVE INGREDIENTS: CARAMEL; SILICON DIOXIDE; LIGHT MINERAL OIL; SODIUM LAURYL SULFATE; CROSPOVIDONE; TALC; STEARIC ACID; MICROCRYSTALLINE CELLULOSE; HYPROMELLOSES; MAGNESIUM STEARATE; POLYETHYLENE GLYCOL 400

0339-CVS

Drug Facts

Active ingredient (in each caplet)

Calcium polycarbophil 625 mg (equivalent to polycarbophil 500 mg)

Purpose

Bulk-forming laxative

Uses

relieves occasional constipation (irregularity)

generally produces bowel movement in 12 to 72 hours

Warnings

Choking: Taking this product without adequate fluid may cause it to swell and block your throat or esophagus and may cause choking. Do not take this product if you have difficulty in swallowing. If you experience chest pain, vomiting, or difficulty in swallowing or breathing after taking this product, seek immediate medical attention

Ask a doctor before use if you have

abdominal pain, nausea, or vomiting

a sudden change in bowel habits that persists over a period of 2 weeks

Ask a doctor or pharmacist before use if you are

taking any other drug. Take this product two or more hours before or after other drugs. Laxatives may affect how other drugs work.

When using this product

do not use for more than 7 days unless directed by a doctor

Stop use and ask a doctor if

you fail to have a bowel movement after use or have rectal bleeding. These could be signs of a serious condition.

Keep out of reach of children.

OVERDOSAGE

In case of overdose, get medical help or contact a Poison Control Center right away.

Directions

take each dose of this product with a full glass of water (8oz.) or other fluid. Taking this product without enough liquid may cause choking. See choking warning.

Adults and children 12 years of age and over | 2 caplets, 1 to 4 times per day. Do not take more than 8 caplets in a 24-hour period unless directed by a doctor.
children under 12 years of age | ask a doctor

Other information

 each caplet contains: calcium 125 mg

do not use if printed seal under cap is torn or missing store in a dry place at 15° – 30°C (59° – 86°F)
protect contents from moisture

Inactive ingredients

caramel, crospovidone, hypromellose, magnesium stearate, microcrystalline cellulose, mineral oil, polyethylene glycol, silicon dioxide, sodium lauryl sulfate, stearic acid, talc.

Questions or comments?

1-800-231-4670

WARNING: This product can expose you to chemicals including lead, which is known to the State of California to cause cancer and birth defects or other reproductive harm. For more information go to www.P65Warnings.ca.gov.

*CVS™ is not affiliated with the owner of the registered trademark FiberCon®.

Distributed by: CVS Pharmacy, Inc.
One CVS Drive, Woonsocket, RI 02895
© 2026 CVS/pharmacy
CVS.com® 1-800-SHOP CVS

PACKAGE LABEL

Compare to FiberCon® active ingredient*

CVS™

NDC 69842-846-02

FIBER LAXATIVE

Plus Calcium

Calcium Polycarbophil, 625 mg

Bulk-Forming Laxative

Fiber Therapy for Regularity

250 CAPLETS